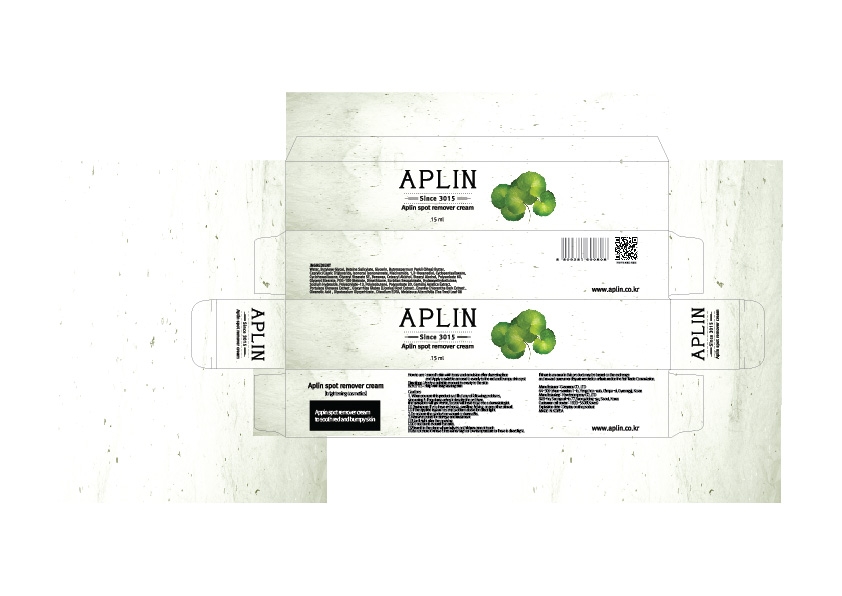 DRUG LABEL: APLIN SPOT REMOVER
NDC: 71079-0002 | Form: CREAM
Manufacturer: Newizcompany
Category: otc | Type: HUMAN OTC DRUG LABEL
Date: 20161117

ACTIVE INGREDIENTS: NIACINAMIDE 2 g/100 mL
INACTIVE INGREDIENTS: GLYCERIN; WATER

Drug Facts

ACTIVE INGREDIENT

NIACINAMIDE

INACTIVE INGREDIENT

WATER, BUTYLENE GLYCOL, GLYCERIN, POLYSORBATE 60, DIMETHICONE, ETC.

PURPOSE

Skin Protectant - Brightening

keep out of reach of the children

INDICATIONS AND USAGE

Apply proper amount to the skin.

WARNINGS

Cautions :

1. When you use this product and find any of following problems, stop using it. if you keep using it despite the problem, the symptom will get worse, so you will have to go see a dermatologist.

(1) During use, if you have red spots, swelling, itching, or any other stimuli.

(2) if the applied region has any problem above for direct light.

2.Do not use the product on wound or dermatitis. 3.Attentive points for storage and treatment :

(1)Use il right after the opening.

(2)Do not use it around eye area.

(3)Store it in the place where infants or children cannot touch. (4)do not store it where it has either high or low temperature or there is direct light.

DOSAGE AND ADMINISTRATION

for external use only